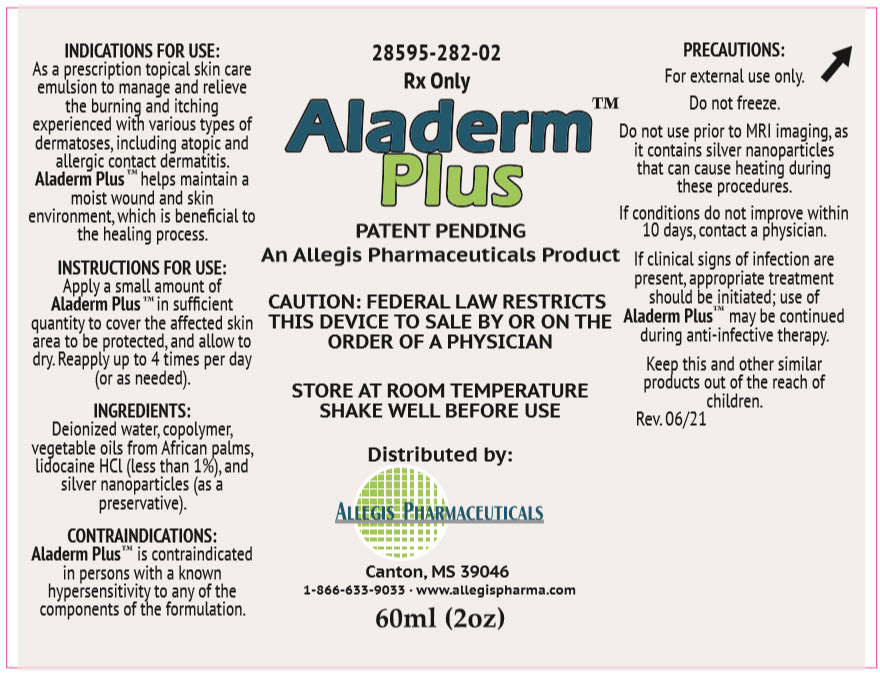 DRUG LABEL: Aladerm Plus
NDC: 328595282022 | Form: EMULSION
Manufacturer: Allegis Pharmaceuticals, LLC
Category: other | Type: PRESCRIPTION MEDICAL DEVICE LABEL
Date: 20230717

Aladerm™
Plus

Rx Only
28595-282-02

DESCRIPTION

Aladerm Plus™ Rx Skin Emulsion is a water-based topical skin care emulsion that is indicated to manage and relieve the burning and itching experienced with various types of dermatoses, including atopic and allergic contact dermatitis.

Aladerm Plus™ Rx Skin Emulsion contains natural extracts to moisturize the skin.

INDICATIONS FOR USE

As a prescription topical skin care emulsion to manage and relieve the burning and itching experienced with various types of dermatoses, including atopic and allergic contact dermatitis. Aladerm Plus™ Rx Skin Emulsion helps maintain a moist wound and skin environment, which is beneﬁcial to the healing process.

CONTRAINDICATIONS

Aladerm Plus™ Rx Skin Emulsion is contraindicated in persons with a known hypersensitivity to any of the components of the formulation.

PRECAUTIONS

Aladerm Plus™ Rx Skin Emulsion is for external use only.

Product should not be used prior to MRI Imaging, as it contains silver nanoparticles that can cause heating during these procedures.

Aladerm Plus™ Rx Skin Emulsion does not contain sunscreen.

If the condition does not improve within 10 days, consult a physician.

If clinical signs of infection are present, appropriate treatment should be initiated; use of Aladerm Plus™

Rx Skin Emulsion may be continued during anti-infective therapy.

Keep this and other similar products out of the reach of children.

DIRECTIONS FOR USE

Apply a small amount of Aladerm Plus™ Rx Skin Emulsion in sufﬁcient quantity to cover the affected skin area to be protected, and allow to dry. Reapply up to 4 times per day (or as needed).

INGREDIENTS

Deionized water, copolymer, vegetable oils from African palms, lidocaine HCl (less than 1%), and silver nanoparticles (as a preservative).

HOW SUPPLIED

Aladerm Plus™ Rx Skin Emulsion is available in a 60 ml bottle.

PRESCRIPTION MEDICAL DEVICE:
FEDERAL LAW RESTRICTS THIS DEVICE TO SALE BY OR ON THE ORDER OF A PHYSICIAN

STORAGE AND HANDLING

SHAKE WELL BEFORE USING

STORE AT ROOM TEMPERATURE

Distributed by:
Allegis Pharmaceuticals, LLC
Canton, MS 39046

QUESTIONS: 1-866-633-9033

PRINCIPAL DISPLAY PANEL - 60 ml Bottle Label

28595-282-02

Rx Only

Aladerm™
Plus

PATENT PENDING
An Allegis Pharmaceuticals Product

CAUTION: FEDERAL LAW RESTRICTS
THIS DEVICE TO SALE BY OR ON THE
ORDER OF A PHYSICIAN

STORE AT ROOM TEMPERATURE
SHAKE WELL BEFORE USE

Distributed by:

ALLEGIS PHARMACEUTICALS

Canton, MS 39046
1-866-633-9033 ∙ www.allegispharma.com

60ml (2oz)